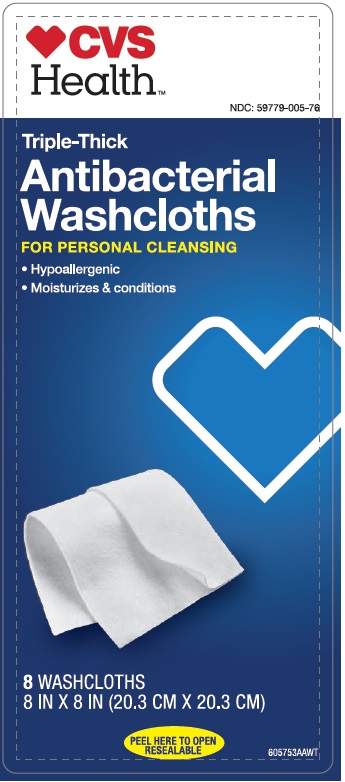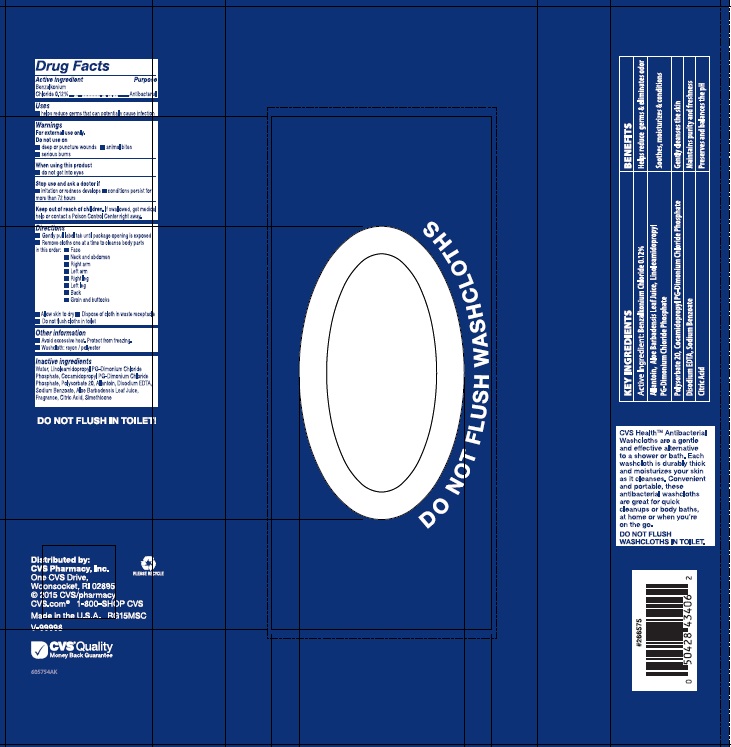 DRUG LABEL: CVS Triple-Thick Antibacterial
NDC: 59779-005 | Form: CLOTH
Manufacturer: CVS Pharmacy
Category: otc | Type: HUMAN OTC DRUG LABEL
Date: 20150924

ACTIVE INGREDIENTS: BENZALKONIUM CHLORIDE 0.12 g/100 mL
INACTIVE INGREDIENTS: ALLANTOIN; ALOE VERA LEAF; ANHYDROUS CITRIC ACID; COCAMIDOPROPYL PROPYLENE GLYCOL-DIMONIUM CHLORIDE PHOSPHATE; EDETATE DISODIUM; LINOLEAMIDOPROPYL PROPYLENE GLYCOL-DIMONIUM CHLORIDE PHOSPHATE; POLYSORBATE 20; DIMETHICONE; SODIUM BENZOATE; WATER

Drug Facts

Active ingredient

Benzalkonium Chloride 0.12%

Purpose

Antibacterial

Uses

- helps reduce germs that can potentially cause infection

Warnings

For external use only.

Do not use on

- deep or puncture wounds
- animal bites
- serious burns

When using this product

- do not get into eyes

Stop use and ask a doctor if

- irritation or redness develops
- conditions persist for more than 72 hours

Keep out of reach of children.

If swallowed, get medical help or contact a Poison Control Center right away.

Directions

Washcloths can be used at room temperature or heated in a microwave for extra comfort.

Heating instructions:

- Place full package in microwave and heat for 45 seconds, then follow washing instructions
- If heating a partial package (2 or more cloths), heat for 15 seconds and test temperature to avoid burning skin.

Washing instructions:

- Gently pull label tab until package opening is exposed
- Remove cloths one at a time to cleanse body parts in this order:
  - Face
  - Neck and abdomen
  - Right arm
  - Left arm
  - Right leg
  - Left leg
  - Back
  - Groin and buttocks
- Allow skin to dry
- Dispose of cloth in waste receptacle
- Do not flush cloths in toilet

Other information

- Avoid excessive heat. Protect from freezing.
- Washcloth: rayon / polyester

Inactive ingredients

Water, Linoleamidopropyl PG-Dimonium Chloride Phosphate, Cocamidopropyl PG-Dimonium Chloride Phosphate, Polysorbate 20, Allantoin, Disodium EDTA, Sodium Benzoate, Aloe Barbadensis Leaf Juice, Fragrance, Citric Acid, Simethicone

Package/Label Principal Display Panel

CVS Health

NDC: 59779-005-76

Triple-thick

ANTIBACTERIAL WASHCLOTHS

FOR PERSONAL CLEANSING

- Hypoallergenic
- Moisturizes & conditions

8 Washcloths

8 in x 8 in (20.3 cm x 20.3 cm)